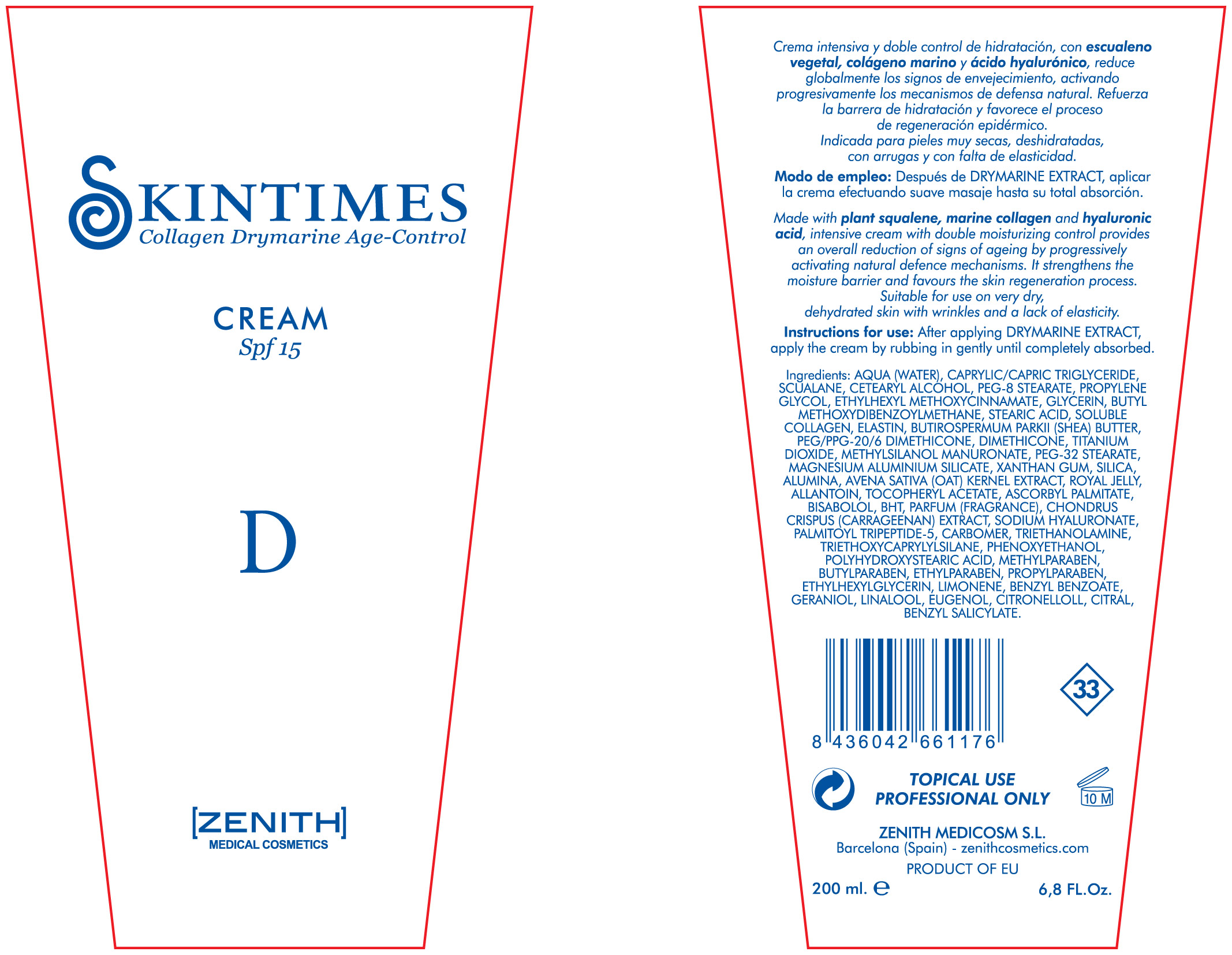 DRUG LABEL: Drymarine
NDC: 42248-123 | Form: CREAM
Manufacturer: Zenith Medicosm SL
Category: otc | Type: HUMAN OTC DRUG LABEL
Date: 20120202

ACTIVE INGREDIENTS: OCTINOXATE 15 mL/200 mL; TITANIUM DIOXIDE 50 mL/200 mL; AVOBENZONE  6 mL/200 mL
INACTIVE INGREDIENTS: MAGNESIUM ALUMINUM SILICATE; PROPYLPARABEN; ALPHA-TOCOPHEROL ACETATE; DIMETHICONE; XANTHAN GUM; TRICAPRYLIN; WATER; SQUALANE; CETOSTEARYL ALCOHOL; PEG-8 STEARATE; TROLAMINE; GLYCERIN; CHONDRUS CRISPUS; BUTYLATED HYDROXYTOLUENE; HYDROLYZED ELASTIN, BOVINE, ALKALINE (1000 MW); CARBOMER 934; SHEA BUTTER; PEG/PPG-20/6 DIMETHICONE; METHYLPARABEN; COLLAGEN, SOLUBLE, FISH SKIN; PEG-32 STEARATE; SILICON DIOXIDE; ALUMINUM OXIDE; STEARIC ACID; OAT; ROYAL JELLY; ASCORBYL PALMITATE; CHONDRUS CRISPUS; HYALURONATE SODIUM; PALMITOYL TRIPEPTIDE-5; ALLANTOIN; TRIETHOXYCAPRYLYLSILANE; LEVOMENOL; PROPYLENE GLYCOL; PHENOXYETHANOL; POLYHYDROXYSTEARIC ACID (2300 MW); BUTYLPARABEN; ETHYLPARABEN; ETHYLHEXYLGLYCERIN; LIMONENE, (+/-)-; BENZYL BENZOATE; GERANIOL; LINALOOL, (+/-)-; EUGENOL; .BETA.-CITRONELLOL, (R)-; CITRAL; BENZYL SALICYLATE

Drug Facts

Active Ingredient

Octinoxate 7.5%

Titanium Dioxide 25%

Avobenzone 3%

Description

Made with plant squalene, marine collagen and hyaluronic acid, intensive cream with double moisturizing control provides an overall reduction of signs of ageing by progressively activating natural defence mechanisms. It strenghtens the moisture barrier and favours the skin regeneration process. Suitable for use on very dry, dehydrated skin with wrinkles and lack of elasticity.

200ml. 6.8 Fl. Oz

Warning

TOPICAL USE

PROFESSIONAL ONLY